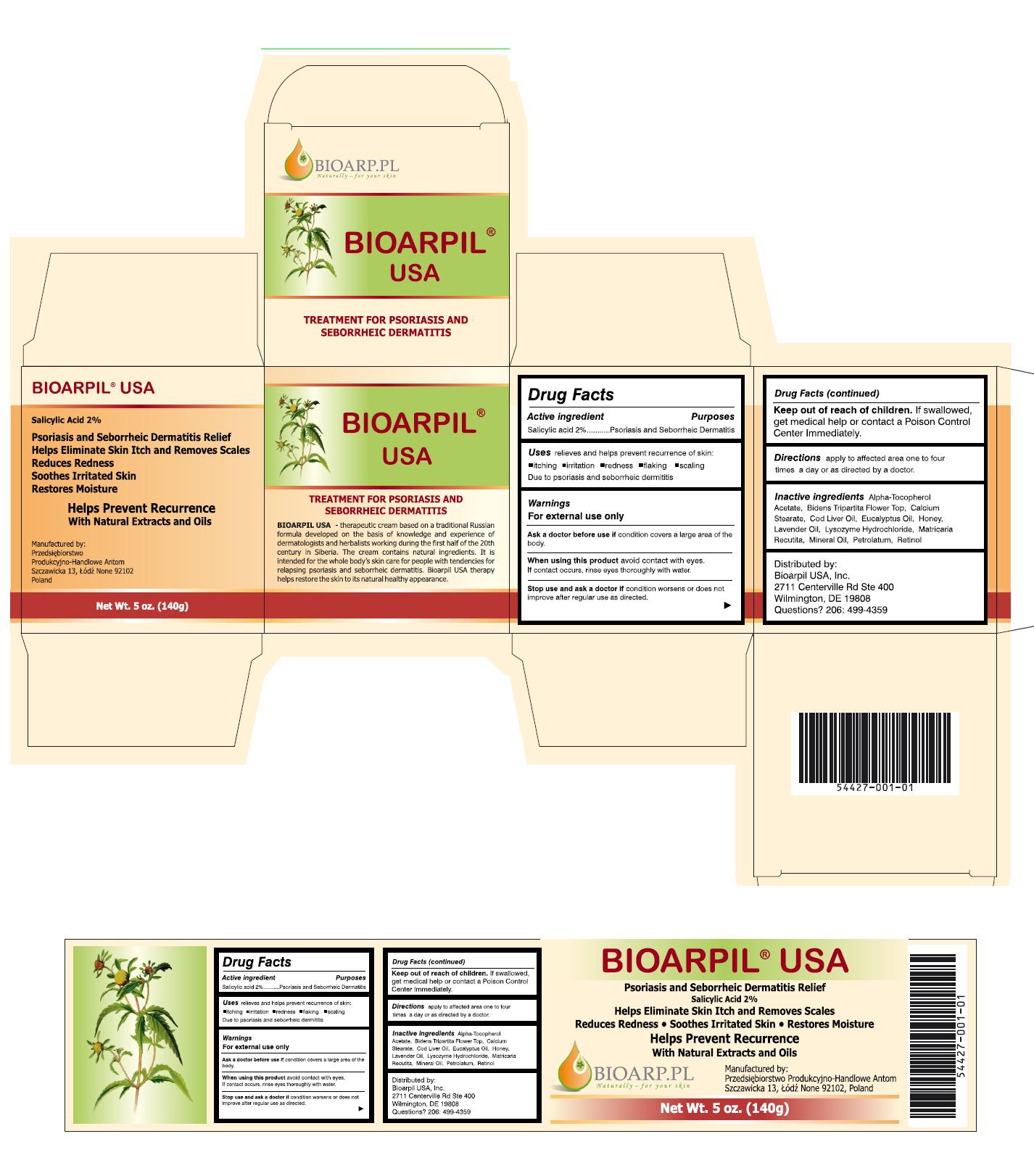 DRUG LABEL: BIOARPIL
NDC: 54427-001 | Form: OINTMENT
Manufacturer: BIOARPIL USA, INC.
Category: otc | Type: HUMAN OTC DRUG LABEL
Date: 20121218

ACTIVE INGREDIENTS: SALICYLIC ACID 2.8 g/140 g
INACTIVE INGREDIENTS: .ALPHA.-TOCOPHEROL ACETATE; BIDENS TRIPARTITA FLOWERING TOP; CALCIUM STEARATE; COD LIVER OIL; EUCALYPTUS OIL; HONEY; LAVENDER OIL; LYSOZYME HYDROCHLORIDE; MATRICARIA RECUTITA; MINERAL OIL; PETROLATUM; RETINOL

Drug Facts

Active Ingredient

Salicylic Acid 2%

Purpose:

psoriasis and seborrheic dermatitis

Keep out of reach of children. If swallowed, get immediate medical help or contact a Poison Control Center immediately.

INDICATIONS AND USAGE

Uses relieves and helps prevent recurrence of skin itching, irritation, redness, flaking, scaling due to psoriasis and seborrheic dermatitis

Warnings

- For external use only
- Ask a doctor before use if condition covers a large part of the body
- When using this product avoid contact with eyes. If contact occurs, rinse eyes thoroughly with water
- Stop use and ask a doctor if condition worsens or does not improve after regular use as directed

Directions

Apply to affected area one to four times daily or as directed by a doctor

Inactive Ingredients

Alpha-Tocopherol Acetate, Bidens Tripartita Flower Top, Calcium Stearate, Cod Liver Oil, Eucalyptus Oil, Honey, Lavender Oil, Lysozyme Hydrochloride, Matricaria Recutita, Mineral Oil, Petrolatum, Retinol.